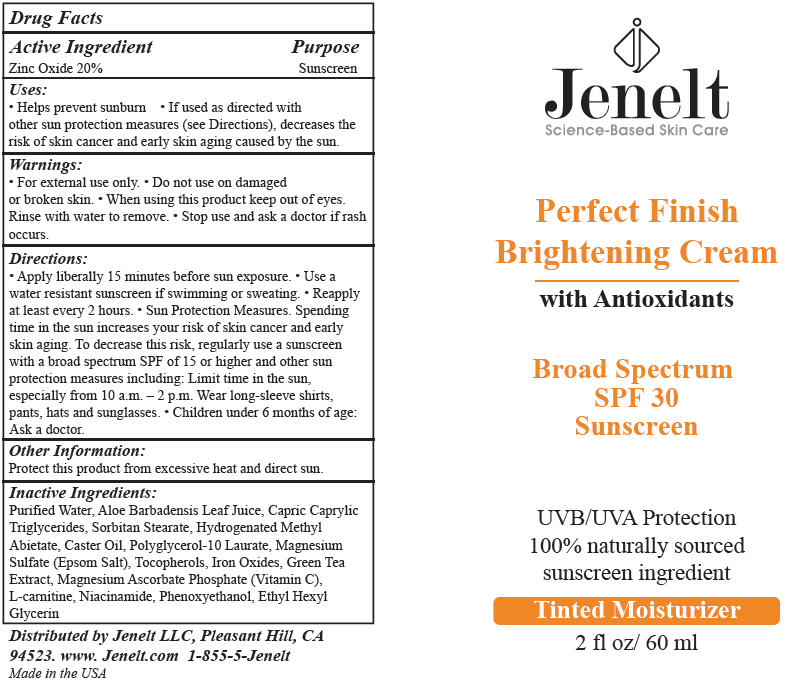 DRUG LABEL: Perfect Finish SPF-30
NDC: 58469-0100 | Form: LOTION
Manufacturer: Jenelt Cosmetics
Category: otc | Type: HUMAN OTC DRUG LABEL
Date: 20150407

ACTIVE INGREDIENTS: Zinc Oxide 20 g/100 mL
INACTIVE INGREDIENTS: WATER; ALOE VERA LEAF; SORBITAN SESQUIOLEATE; HYDROGENATED CASTOR OIL; POLYGLYCERYL-10 LAURATE; MAGNESIUM SULFATE; Hydrogenated Methyl Abietate; green tea leaf; MAGNESIUM ASCORBYL PHOSPHATE; carnitine; TOCOPHEROL; niacinamide; glycerin; PHENOXYETHANOL; ETHYLHEXYLGLYCERIN; FERRIC OXIDE RED

Perfect Finish SPF-30

Drug Facts

Active Ingredient

Zinc Oxide 20%

Purpose

Sunscreen

Uses

- Helps prevent sunburn
- If used as directed with other sun protection measures (see Directions), decreases the risk of skin cancer and early skin aging caused by the sun.

Warnings

- For external use only.

- Do not use on damaged or broken skin.

- When using this product keep out of eyes. Rinse with water to remove.

- Stop use and ask a doctor if rash occurs.

Directions

- Apply liberally 15 minutes before sun exposure.
- Use a water resistant sunscreen if swimming or sweating.
- Reapply at least every 2 hours.
- Sun Protection Measures. Spending time in the sun increases your risk of skin cancer and early skin aging. To decrease this risk, regularly use a sunscreen with a broad spectrum SPF of 15 or higher and other sun protection measures including: Limit time in the sun, especially from 10 a.m. – 2 p.m. Wear long-sleeve shirts, pants, hats and sunglasses.
- Children under 6 months of age: Ask a doctor.

Other Information

Protect this product from excessive heat and direct sun.

Inactive Ingredients

Purified Water, Aloe Barbadensis Leaf Juice, Capric Caprylic Triglycerides, Sorbitan Stearate, Hydrogenated Methyl Abietate, Caster Oil, Polyglycerol-10 Laurate, Magnesium Sulfate (Epsom Salt), Tocopherols, Iron Oxides, Green Tea Extract, Magnesium Ascorbate Phosphate (Vitamin C), L-carnitine, Niacinamide, Phenoxyethanol, Ethyl Hexyl Glycerin

Distributed by Jenelt LLC, Pleasant Hill, CA
94523.

PRINCIPAL DISPLAY PANEL - 60 ml Tube Label

Jenelt
Science-Based Skin Care

Perfect Finish
Brightening Cream

with Antioxidants

Broad Spectrum
SPF 30
Sunscreen

UVB/UVA Protection
100% naturally sourced
sunscreen ingredient

Tinted Moisturizer

2 fl oz/ 60 ml